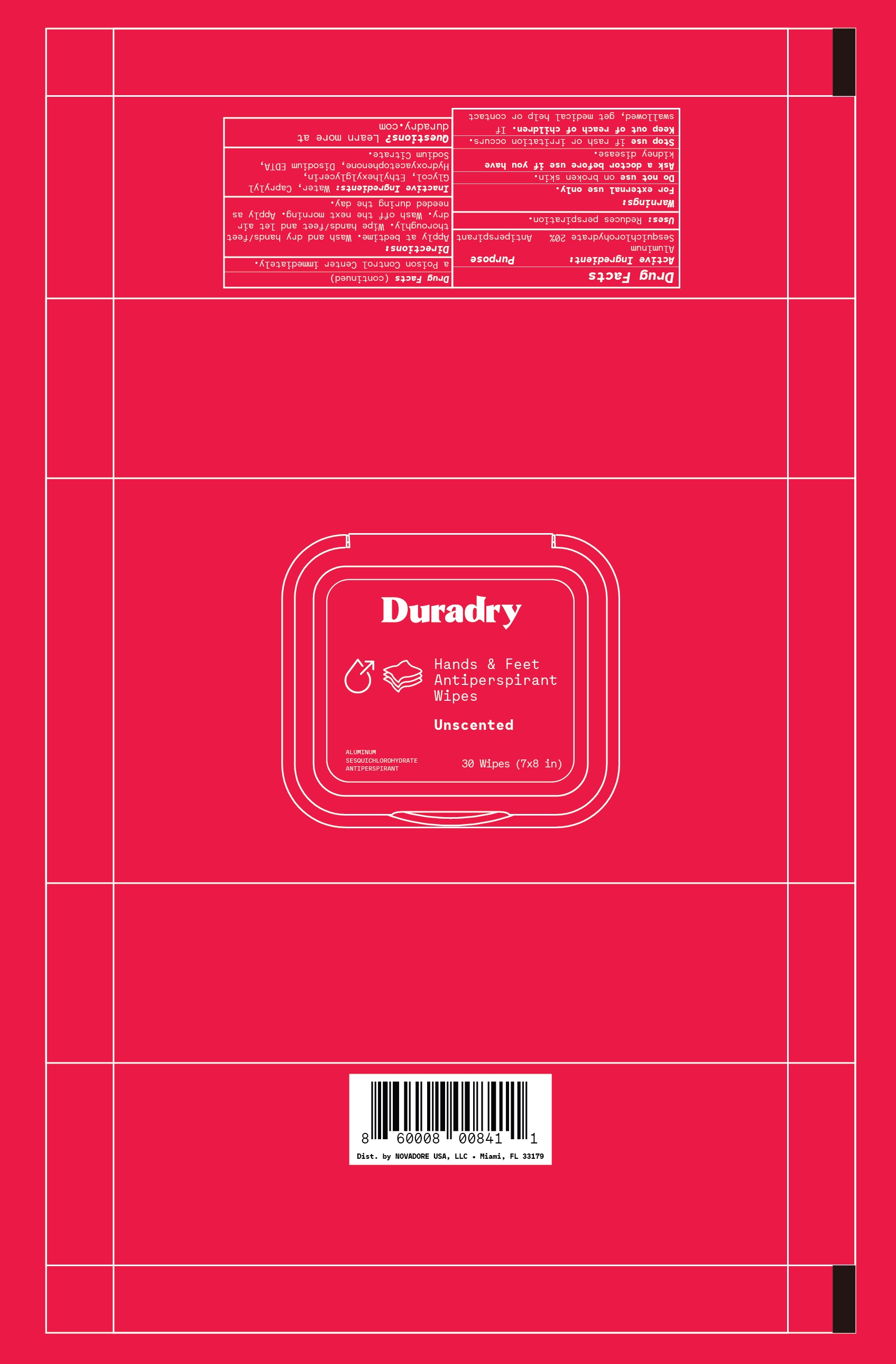 DRUG LABEL: Duradry Hands and Feet Antiperspirant Wipes
NDC: 69990-400 | Form: CLOTH
Manufacturer: Novadore USA Inc
Category: otc | Type: HUMAN OTC DRUG LABEL
Date: 20240112

ACTIVE INGREDIENTS: ALUMINUM SESQUICHLOROHYDRATE 200 mg/1 mL
INACTIVE INGREDIENTS: EDETATE DISODIUM; SODIUM CITRATE; WATER; CAPRYLYL GLYCOL; ETHYLHEXYLGLYCERIN; HYDROXYACETOPHENONE

Duradry Hands and Feet Antiperspirant Wipes

Active Ingredient

Aluminum Sesquichlorohydrate 20%

Purpose

Antiperspirant

Uses

Reduces perspiration

Warnings

For external use only.

Do not use

on broken skin

Ask a doctor before use

if you have kidney disease.

Keep out of reach of children

If swallowed, get medical help or contact a Poison Control Center immediately.

Stop use

if rash or irritation occurs.

Directions

Apply at bedtime. Wash and dry hands/feet thoroughly. Wipe hands/feet and let air dry. Wash off the next morning. Apply as needed during the day.

Inactive ingredients

Water, Caprylyl Glycol, Ethylhexylglycerin, Hydroxyacetophenone, Disodium EDTA, Sodium Citrate.

Questions?

Learn more at duradry.com

Dist. by Novadore USA LLC

Miami, FL 33179